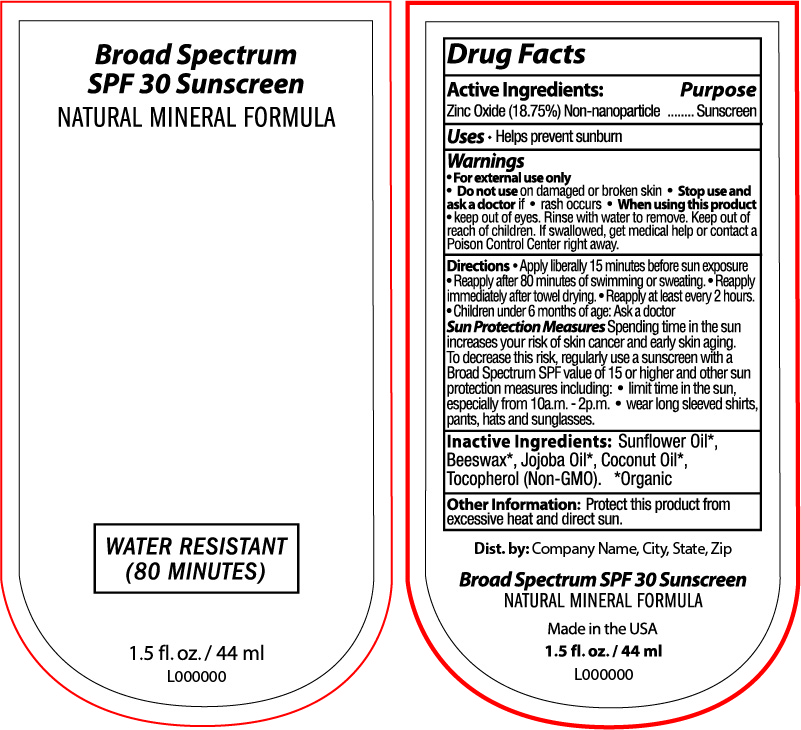 DRUG LABEL: Broad Spectrum SPF 30 Sunscreen
NDC: 65692-0566 | Form: LOTION
Manufacturer: Raining Rose
Category: otc | Type: HUMAN OTC DRUG LABEL
Date: 20231018

ACTIVE INGREDIENTS: ZINC OXIDE 8.25 g/44 mL
INACTIVE INGREDIENTS: WHITE WAX; JOJOBA OIL; TOCOPHEROL; COCONUT OIL; SUNFLOWER OIL

Broad Spectrum SPF 30 Mineral Sunscreen 1.5 fl oz

Active Ingredients:

Zinc Oxide (18.75%) Non-nanoparticle

Purpose:

Sunscreen

Uses:

- Helps prevent sunburn

Warnings:

- For external use only
- Do not use on damaged or broken skin
- Stop use and ask a doctor if rash occurs
- When using this product keep out of eyes. Rinse with water to remove.

KEEP OUT OF REACH OF CHILDREN

Keep out of readh of children. If swallowed, get medical help or contact a Poison Control Center right away.

Directions

- Apply liberally 15 minutes before sun exposure
- Reapply after 80 minutes of swimming or sweating
- Reapply immediately after towel drying
- Reapply at least every 2 hours
- Children under 6 months of age: Ask a doctor

Sun Protection Measures Spending time in the sun increases your risk of skin cancer and early skin aging. To decrease this risk, regularly use a sunscreen with a Broad Spectrum SPF value of 15 or higher and other sun protection measures including:

- Limit time in the sun, especially from 10a.m.-2p.m.
- wear long sleeved shirts, pants, hats and sunglasses.

Other Information

Protect this product from excessive heat and direct sun.

Inactive Ingredients

Sunflower Oil*, Beeswax*, Jojoba Oil*, Coconut Oil*, Tocopherol (Non-GMO). *Organic

INDICATIONS AND USAGE

Helps prevent sunburn

DOSAGE AND ADMINISTRATION

Apply liberally 15 minutes before sun exposure

PACKAGE LABEL

Broad Spectrum SPF 30 Sunscreen

Natural Mineral Formula

Water Resistant

(80 minutes)

1.5 fl.oz./44 mL